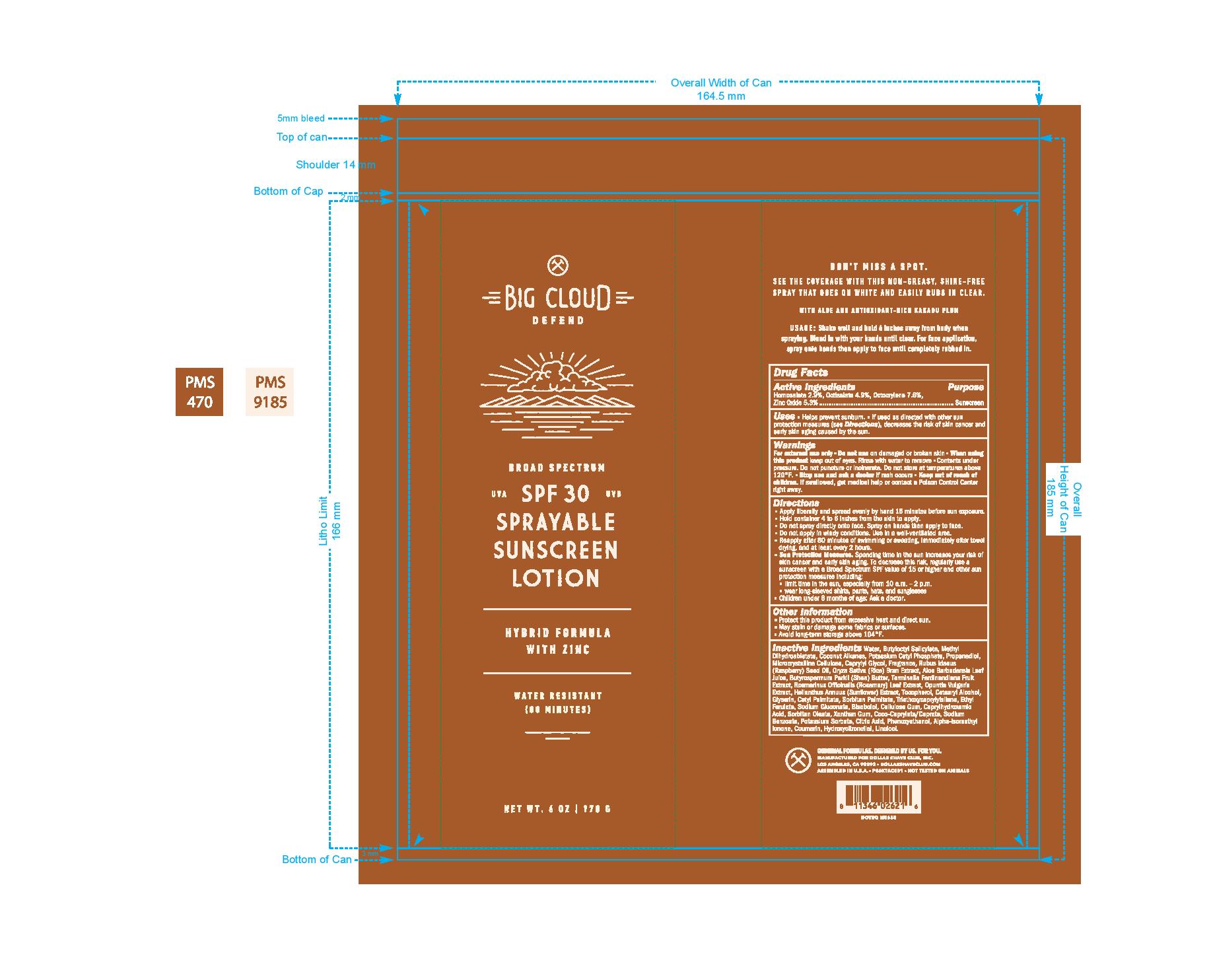 DRUG LABEL: Big Cloud Defend
NDC: 76150-244 | Form: SPRAY, SUSPENSION
Manufacturer: Bell International Laboratories, Inc.
Category: otc | Type: HUMAN OTC DRUG LABEL
Date: 20200501

ACTIVE INGREDIENTS: OCTOCRYLENE 7.6 g/100 g; OCTISALATE 4.9 g/100 g; HOMOSALATE 2.9 g/100 g; ZINC OXIDE 5.3 g/100 g
INACTIVE INGREDIENTS: GLYCERIN; PHENOXYETHANOL; LEVOMENOL; CETYL PALMITATE; METHYL DIHYDROABIETATE; RICE BRAN; HELIANTHUS ANNUUS FLOWERING TOP; ALOE VERA LEAF; PRICKLY PEAR FRUIT; SODIUM BENZOATE; POTASSIUM CETYL PHOSPHATE; CAPRYLYL GLYCOL; BUTYLOCTYL SALICYLATE; RASPBERRY SEED OIL; PROPANEDIOL; POTASSIUM SORBATE; CITRIC ACID MONOHYDRATE; ROSEMARY; TOCOPHEROL; CETOSTEARYL ALCOHOL; SORBITAN MONOPALMITATE; SORBITAN MONOOLEATE; TRIETHOXYCAPRYLYLSILANE; SHEA BUTTER; SODIUM GLUCONATE; CAPRYLHYDROXAMIC ACID; XANTHAN GUM; MICROCRYSTALLINE CELLULOSE; CARBOXYMETHYLCELLULOSE SODIUM, UNSPECIFIED FORM; WATER

Dollar Shave Club Big Clound Defend SPF 30 Sprayable Sunscreen Lotion

Active Ingredient

Homosalate 2.9%, Octisalate 4.9%, Octocrylene 7.6%, Zinc Oxide 5.3%

Purpose

Sunscreen

Uses

Helps prevent sunburn.

If used as directed with other sun protection measures (see Directions), decreases the risk of skin cancer and early skin aging caused by the sun.

Warnings

For external use only

Do not use on damaged or broken skin

when using this product keep out of eyes. Rinse with water to remove

Contents under pressure. Do not puncture or incinerate. Do not store at temperatures above 120 oF.

Stop use and ask a doctor if rash occurs

Keep out of reach of children. If swallowed, get medical help or contact a Poison Control Center right away.

Directions

Apply liberally and spread evenly by hand 15 minutes before sun exposure.

hold container 4 to 6 inches from the skin to apply.

do not spray directly onto face. Spray onto hands then apply to face

do not apply in windy conditions. Use in a well-ventilated area.

Reapply after 80 minutes of swimming or sweating, immediately after towel drying, and at least every 2 hours

Sun Protection Measures. Spending time in the sun increases your risk of skin cancer and early skin aging. To decrease this risk, regularly use a sunscreen wtih a broad spectrum SPF value of 15 or higher and other sun protection measures including: Limit time in the sun, especially from 10am-2pm. Wear logn-sleeved shirts, pants, hats, and sunglasses.

Children under 6 months of age: Ask a doctor

Other Information

Protect this product from excessive heat and direct sun.

May stain or damage some fabrics or surfaces

Avoid long-term storage above 104 oF

Inactive Ingredients

water, butyloctyl salicylate, methyl dihydroabietate, coconut alkanes, potassium cetyl phosphate, propanediol, microcrystalline cellulose, caprylyl glycol, fragrance, rubus ideaus (raspberry) seed oil, oryza sativa (rice) bran extract, aloe barbadensis leaf juice, butyrospermum parkii (shea) butter, terminalia ferdinandiana fruit extract, rosmarinus officinalis (rosemary) leaf extract, opuntia vulgaris extract, helianthus annuus (sunflower) extract, tocopherol, cetearyl alcohol, glycerin, cetyl palmitate, sorbitan palmitate, triethoxycaprylylsilane, ethyl ferulate, sodium gluconate, bisabolol, cellulose gum, caprylylhydroxamic acid, sorbitan oleate, xanthan gum, coco-caprylate/caprate, sodium benzoate, potassium sorbate, citric acid, phenoxyethanol, Alpha-Isomethyl Ionone, Coumerin, Hydroxyitronellal, Linalool